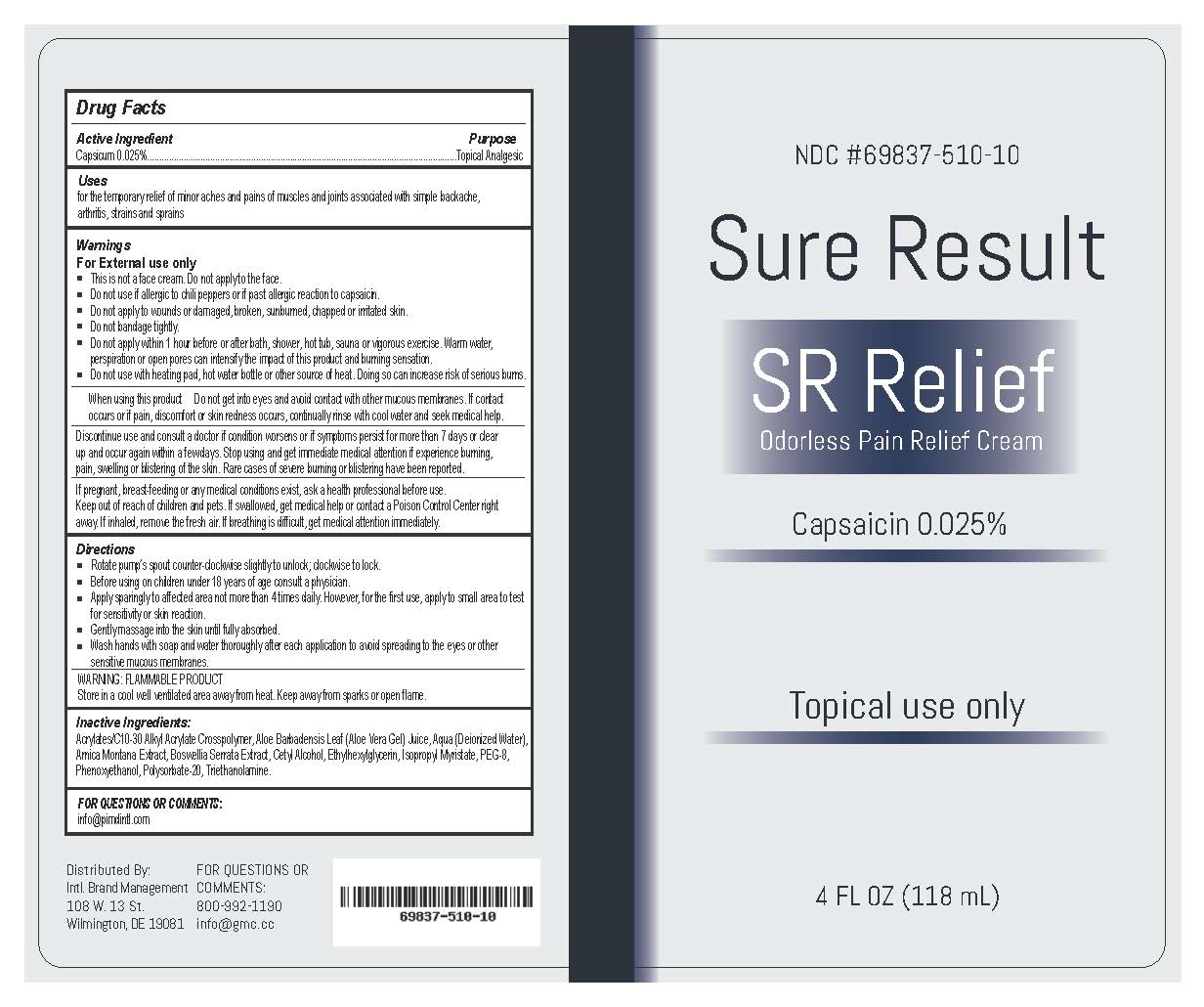 DRUG LABEL: Sure Result SR Relief
NDC: 69837-510 | Form: CREAM
Manufacturer: International Brand Management, LLC
Category: otc | Type: HUMAN OTC DRUG LABEL
Date: 20170623

ACTIVE INGREDIENTS: CAPSAICIN .025 mg/.001 g
INACTIVE INGREDIENTS: (C10-C30)ALKYL METHACRYLATE ESTER; ALOE VERA LEAF; WATER; ARNICA MONTANA; BOSWELLIA SERRATA RESIN OIL; CETYL ALCOHOL; ETHYLHEXYLGLYCERIN; ISOPROPYL MYRISTATE; POLYETHYLENE GLYCOL 800; PHENOXYETHANOL; POLYSORBATE 20; TRIETHANOLAMINE GLUTAMATE

Drug Facts

Active Ingredient

Capsaicin 0.025%

Purpose

Topical Analgesic

Uses

for the temporary relief of minor aches and painsof muscles and joints associated with a simple backache,

athritis, strains and sprains

Warnings

For external use only

- This is not a face cream. Do not apply to the face.
- Do not use if allergic to chili peppers or if past allergic reaction to capsaicin
- Do not apply to wounds or damaged, broken, sunburned, chapped or irritated skin.
- Do not bandage tightly
- Do not apply within 1 hour before or after bath, shower, hot tub, saunaor vigrous exercise
- Warm water, perspiration or open pores can intensify the impact of this product and bruning sensation.
- Do not use with heating pad, hot water bottle or other source of heat. Doing so can increase risk of serious burns.

When using this product Do not get into eyesand avoid contact with mucous membranes. If contact

occurs or if pain, discomfort or skin redness occurs, continuously rinse with cool water and seek medical help.

Discontinue use and consult a doctor if condition worsens or if symptoms persist for more than 7 days or clear

up and occur again within a few days. Stop using and get immediate medical attention if experience burning,

pain, swelling or blistering of the skin. Rare cases of severe burning or blistering have been reported.

KEEP OUT OF REACH OF CHILDREN

If pregnant, breast-feeding or any medical conditions exist, ask a health professional before use.

Keep out of reach of children and pets. If swallowed, get medical help or contact a Poison Control Center right away.

If inhaled, remove the fresh air. If breathing is difficult, get medical attention immediately.

Directions

- Rotate pump's spout counter-clockwise slightly to unlock; clockwise to lock.
- Before using on children under 18 years of age consult a physician.
- Apply sparingly to affected area not more than 4 times daily. However, for the first use, apply to small area to test for sensitivity or skin reaction.
- Gently massage into skin until fully absorbed.
- Wash hands with soap and water thoroughly after each applicationto avoid spreading to the eyes or other sensitive mucous membranes.

STORAGE AND HANDLING

WARNING: FLAMMABLE PRODUCT

Store in a cool well ventilated area away from heat. Keep away from sparks or open flame.

Inactive Ingredients

Acrylates/C10-30 Alkyl Acrylate Crosspolymer, Aloe Barbadensis Leaf (Aloe Vera Gel) Juice,

Aqua (Deionized Water), Arnica Montana Extract, Bosswellia Serrata Extract,

Cetyl Alcohol, Ethylhexylglycerin, Isopropyl Myristate, PEG-8,

Phenoxyethanol, Polysorbate-20, Triethanolamine

FOR QUESTIONS OR COMMENTS:

info@pindintl.com